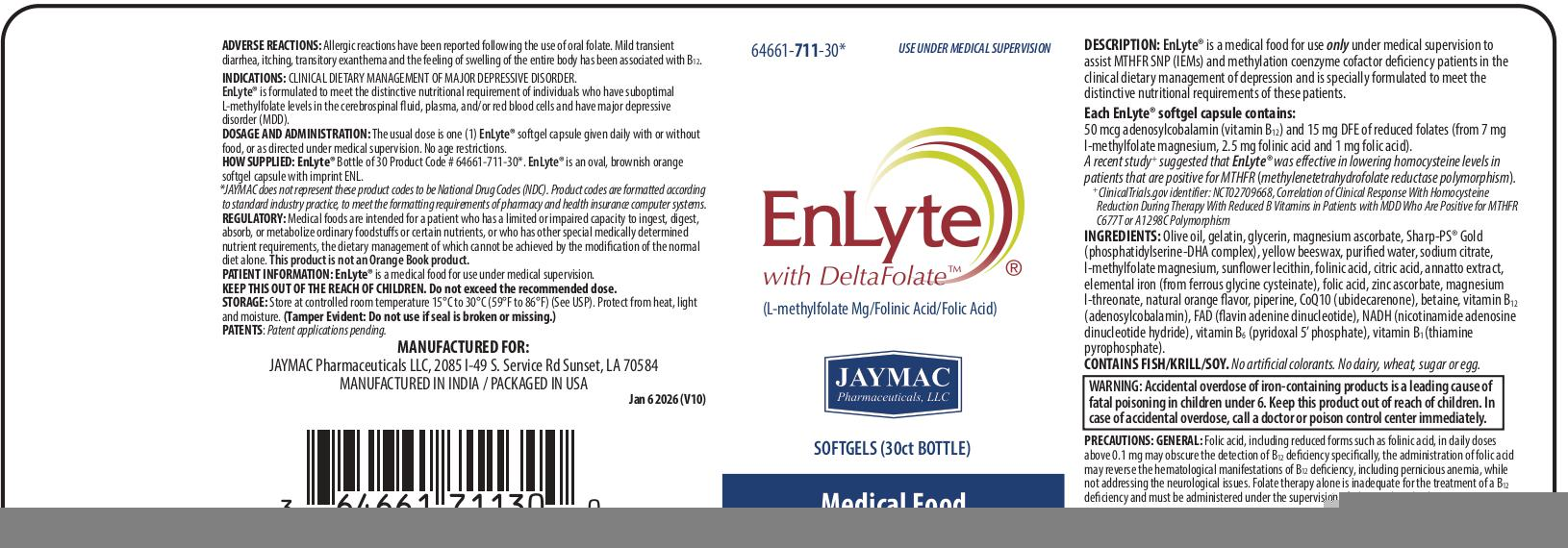 DRUG LABEL: EnLyte
NDC: 64661-711 | Form: CAPSULE, DELAYED RELEASE PELLETS
Manufacturer: Jaymac Pharma
Category: other | Type: MEDICAL FOOD
Date: 20260122

ACTIVE INGREDIENTS: LEUCOVORIN 2.5 mg/1 1; FOLIC ACID 1 mg/1 1; LEVOMEFOLATE MAGNESIUM 7 mg/1 1; FERROUS CYSTEINE GLYCINATE 13.6 mg/1 1; 1,2-DOCOSAHEXANOYL-SN-GLYCERO-3-PHOSPHOSERINE CALCIUM 6.4 mg/1 1; 1,2-ICOSAPENTOYL-SN-GLYCERO-3-PHOSPHOSERINE CALCIUM 800 ug/1 1; PHOSPHATIDYL SERINE 12 mg/1 1; PYRIDOXAL PHOSPHATE ANHYDROUS 25 ug/1 1; FLAVIN ADENINE DINUCLEOTIDE 25 ug/1 1; NADH 25 ug/1 1; COBAMAMIDE 50 ug/1 1; COCARBOXYLASE 25 ug/1 1; MAGNESIUM ASCORBATE 24 mg/1 1; ZINC ASCORBATE 1 mg/1 1; MAGNESIUM L-THREONATE 1 mg/1 1; BETAINE 500 ug/1 1; CITRIC ACID MONOHYDRATE 1.83 mg/1 1; SODIUM CITRATE 3.67 mg/1 1
INACTIVE INGREDIENTS: ANNATTO; GELATIN; GLYCERIN; LECITHIN, SUNFLOWER; OLIVE OIL; PIPERINE; WATER; UBIDECARENONE; YELLOW WAX

EnLyte® with DeltaFolateTM

EnLyte®

with DeltaFolate™

[15 mg DFE]

JAYMAC Pharmaceuticals, LLC

Softgels (30ct bottle)

Medical FoodFor Therapeutic Use

Description

EnLyte® is a medical food for use only under medical supervision to assist MTHFR SNP (IEMs) and methylation coenzyme cofactor deficiency patients in the clinical dietary management of depression and is specially formulated to meet the distinctive nutritional requirements for these patients.

Each EnLyte® softgel capsule contains: 50 mcg adenosylcobalamin (vitamin B12) and 15 mg DFE of reduced folates (from 7 mg l-methylfolate magnesium, 2.5 mg folinic acid, and 1 mg folic acid).

A recent study^+ suggested that EnLyte® was effective in lowering homocystine levels in patients that are positive for MTHFR (methylenetetrahydrofolate reductase polymorphism).

^+ClinicalTrials.gov identifier: NCT02709668, Correlation of Clinical Response With Homocysteine Reduction During Therapy With Reduced B Vitamins in Patients with MDD Who Are Posititive for MTHFR C677T or A1298C Polymorphism.

Ingredients: Olive oil, gelatin, glycerin, magnesium ascorbate, Sharp-PS® Gold (phosphatidylserine-DHA complex), yellow beeswax, purified water, sodium citrate, l-methylfolate magnesium, sunflower lecithin, folinic acid, citric acid, annatto extract, elemental iron (from ferrous glycine cysteinate), folic acid, zinc ascorbate, magnesium l-threonate, natural orange flavor, piperine, CoQ10 (ubidecarenone), betaine, vitamin B12 (adenosylcobalamin), FAD (flavin adenine dinucleotide), NADH (nicotinamide adenosine dinucleotide hydride), vitamin B6 (pyridoxal 5’ phosphate), vitamin B1 (thiamine pyrophosphate).

CONTAINS FISH/KRILL/SOY. No artificial colorants. No dairy, wheat, sugar or egg.

Medical foods are intended for a patient who has a limited or impaired capacity to ingest, digest, absorb, or metabolize ordinary foodstuffs or certain nutrients, or who has other special medically determined nutrient requirements, the dietary management of which cannot be achieved by the modification of the normal diet alone.

INDICATIONS:

CLINICAL DIETARY MANAGEMENT OF MAJOR DEPRESSIVE DISORDER.

ADVERSE REACTIONS:

Allergic reactions have been reported following the use of oral folate. Mild transient diarrhea, itching, transitory exanthema and the feeling of swelling of the entire body has been associated with B12.

PRECAUTIONS:

Folic acid, including reduced forms such as folinic acid, in daily doses above 0.1 mg may obscure the detection of B12 deficiency specifically, the administration of folic acid may reverse the hematological manifestations of B12 deficiency, including pernicious anemia, while not addressing the neurological issues. Folate therapy alone is inadequate for the treatment of a B12 deficiency and must be administered under the supervision of a licensed medical practitioner.

DOSAGE AND ADMINISTRATION:

The usual dose is one EnLyte® softgel capsule given daily with or without food, or as directed under medical supervision. No age restrictions.

KEEP THIS OUT OF THE REACH OF CHILDREN.

Do not exceed the recommended dose.

HOW SUPPLIED:

Oval, brownish orange softgel capsule with imprint ENL.

STORAGE:

Store at controlled room temperature 15°C to 30°C (59°F to 86°F) (See USP).

Protect from heat, light and moisture.

(Tamper Evident: Do not use if seal is broken or missing.)

JAYMAC Pharmaceuticals LLC, 2085 I-49 S. Service Rd, Sunset, LA 70584

MANUFACTURED IN INDIA / PACKAGED IN USA.

Jan 6 2026 (V10)

WARNING:

Accidental overdose of iron-containing products is a leading cause of fatal poisoning in children under 6. Keep this product out of reach of children. In case of accidental overdose, call a doctor or poison control center immediately.